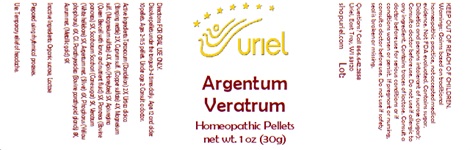 DRUG LABEL: Argentum Veratrum
NDC: 48951-1358 | Form: PELLET
Manufacturer: Uriel Pharmacy, Inc.
Category: homeopathic | Type: HUMAN OTC DRUG LABEL
Date: 20241217

ACTIVE INGREDIENTS: PHOSPHORUS 6 [hp_X]/1 1; APIS MELLIFERA 5 [hp_X]/1 1; BOS TAURUS PARATHYROID GLAND 8 [hp_X]/1 1; TARAXACUM PALUSTRE ROOT 2 [hp_X]/1 1; SILVER 6 [hp_X]/1 1; GOLD 9 [hp_X]/1 1; CUPRIC SULFATE 4 [hp_X]/1 1; SUS SCROFA PANCREAS 5 [hp_X]/1 1; SUGARCANE 5 [hp_X]/1 1; URTICA DIOICA 2 [hp_X]/1 1; MAGNESIUM SULFATE, UNSPECIFIED 4 [hp_X]/1 1; ROYAL JELLY 5 [hp_X]/1 1; VERATRUM ALBUM ROOT 5 [hp_X]/1 1
INACTIVE INGREDIENTS: SUCROSE; LACTOSE, UNSPECIFIED FORM

Argentum Veratrum

INDICATIONS AND USAGE

Directions: FOR ORAL USE ONLY.

DOSAGE AND ADMINISTRATION

Dissolve pellets under the tongue 3-4 times daily. Ages 12 and older: 10 pellets. Ages 2-11: 5 pellets. Under age 2: Consult a doctor.

ACTIVE INGREDIENT

Active Ingredients: Taraxacum (Dandelion) 2X, Urtica dioica (Stinging nettle) 2X, Cuprum sulf. (Copper sulfate) 4X, Magnesium sulf. (Magnesium sulfate) 4X, Apis (Honeybee) 5X, Apis regina (Queen Bee cell with larva and nutrient fluid) 5X, Pancreas (Bovine pancreas) 5X, Saccharum Sacchari (Cane sugar) 5X, Veratrum (White hellebore) 5X, Argentum met. (Silver) 6X, Phosphorus (Yellow phosphorus) 6X, Gl. Parathyreoidea (Bovine parathyroid glands) 8X, Aurum met. (Metallic gold) 9X

Inactive Ingredients: Organic sucrose, Lactose

Prepared using rhythmical processes.

PURPOSE

Use: Temporary relief of headache..

KEEP OUT OF REACH OF CHILDREN.

WARNINGS

Warnings: Claims based on traditional homeopathic practice, not accepted medical evidence. Not FDA evaluated. Contains sugar. Diabetics and persons intolerant of sucrose (sugar): Consult a doctor before use. Do not use if allergic to any ingredient. Contains traces of lactose. Consult a doctor before use for serious conditions or if conditions worsen or persist. If pregnant or nursing, consult a doctor before use. Do not use if safety seal is broken or missing.

Questions? Call 866.642.2858
Uriel, East Troy, WI 53120
shopuriel.com Lot: